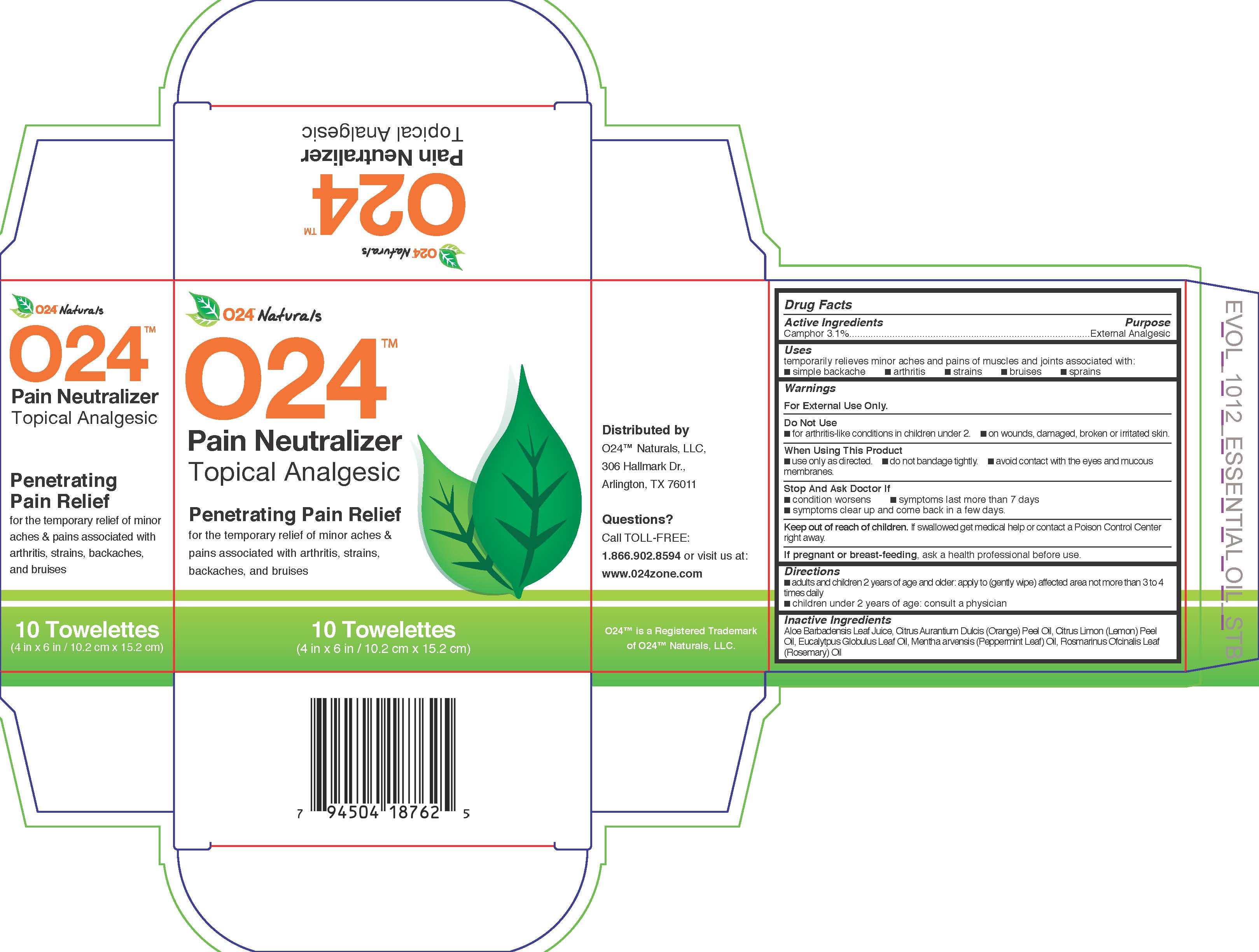 DRUG LABEL: O24 Pain Neutralizer
NDC: 72608-004 | Form: LIQUID
Manufacturer: D&d Essential Oils, Llc.,
Category: otc | Type: HUMAN OTC DRUG LABEL
Date: 20181014

ACTIVE INGREDIENTS: CAMPHOR (NATURAL) 3.1 g/100 g
INACTIVE INGREDIENTS: ROSEMARY OIL; ALOE VERA LEAF; ORANGE OIL; LEMON OIL; EUCALYPTUS OIL; MENTHA ARVENSIS FLOWER OIL

ACTIVE INGREDIENT

Camphor 3.1%

PURPOSE

Camphor 3.1%.............................External Analgesic

INDICATIONS AND USAGE

temporarily relieves minor aches and pains of muscles and joints associated with:

- simple backache
- arthritis
- strains
- bruises
- sprains

WARNINGS

For External Use Only.

Do Not Use

- For arthritis-like conditions in children under 2.
- on wounds, damaged, broken or irritated skin.

When Using This Product

- use only as directed.
- do not bandage tightly.
- avoid contact with the eyes and mucous membranes.

Stop Use and Ask Doctor If

- condition worsens
- symptoms last more than 7 days
- symptoms clear up and come back in a few days

KEEP OUT OF REACH OF CHILDREN

Keep our of reach of children. If swallowed get medical help or contact a Poison Control Center right away.

PREGNANCY OR BREAST FEEDING

If pregnant or breast-feeding, ask a health professional before use.

DOSAGE AND ADMINISTRATION

- adults and children 2 years of age and older: apply to (gently wipe) affected area not more than 3 to 4 times daily
- children under 2 years of age: consult a physician

INACTIVE INGREDIENT

Aloe Barbadensis Leaf Juice, Citrus Aurantium Dulcis (Orange) Peel Oil, Citrus Limon (Lemon) Peel Oil, Eucalyptus Globulus Leaf Oil, Mentha arvensis (Peppermint Leaf) Oil, Rosmarinus Ofcinalis Leaf (Rosemary) Oil

DESCRIPTION

Distributed by

O24TM Naturals, LLC

306 Hallmark Dr.,

Arlington, TX 76011

Questions?

Call TOLL-FREE:

1.866.902.8594 or visit us at:

www.O24zone.com

O24TM is a Registered Trademark

of O24TM Naturals, LLC.

PACKAGE LABEL

024TM Naturals

024TM

Pain Neutralizer

Topical Analgesic

Penetrating Pain Relief

for the temporary relieft of minor aches & pains associated with arthritis, strains, backaches, and bruises

10 Towelettes

(4 in x 6 in / 10.2 cm x 15.2 cm)